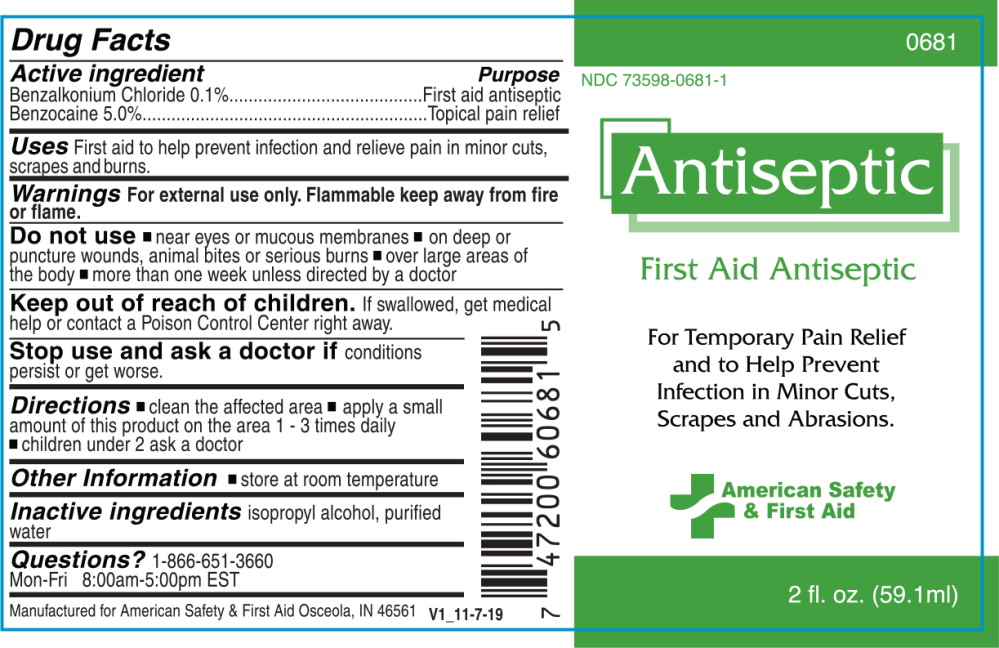 DRUG LABEL: Antiseptic
NDC: 73598-0681 | Form: SPRAY
Manufacturer: JHK Inc
Category: otc | Type: HUMAN OTC DRUG LABEL
Date: 20240425

ACTIVE INGREDIENTS: benzalkonium chloride 100 mg/1 mL; benzocaine 50 mg/1 mL
INACTIVE INGREDIENTS: isopropyl alcohol; water

Drug Facts

Active Ingredient

Benzalkonium Chloride 0.1%

Benzocaine 5.0%

Purpose

First aid antiseptic

Topical pain relief

Uses

First aid to help prevent infection and relieve pain in minor cuts, scrapes and burns.

Warnings

For external use only. Flammable keep away from fire or flame.

Do not use

- near eyes or mucous membranes
- on deep or puncture wounds, animal bites or serious burns
- over large areas of the body
- more than one week unless directed by a doctor

Keep out of reach of children. If swallowed, get medical help or contact a Poison Control Center right away.

Stop use and ask a doctor if conditions persist or get worse.

Directions

- clean the affected area
- apply a small amount of this product on the area 1 - 3 times daily
- children under 2 ask a doctor

Other Information

- store at room temperature

Inactive ingredients

isopropyl alcohol, purified water

Questions?

1-866-651-3660

Mon-Fri 8:00am-5:00pm EST

Manufactured for American Safety & First Aid Osceola, IN 48561

V1_11-7-19

Principal Display Panel – Bottle Label

0681

NDC 73598-0681-1

Antiseptic

First Aid Antiseptic

For Temporary Pain Relief
and to Help Prevent
Infection in Minor Cuts,
Scrapes and Abrasions

American Safety
& First Aid

2 fl. Oz. (59.1 ml)